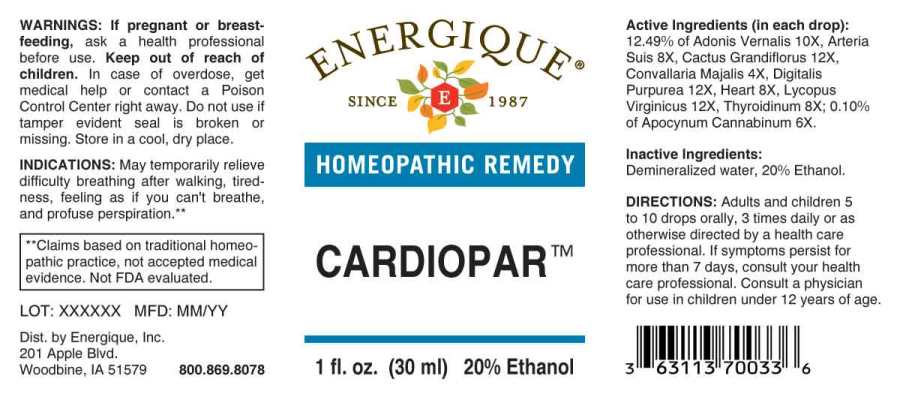 DRUG LABEL: Cardiopar
NDC: 44911-0532 | Form: LIQUID
Manufacturer: Energique, Inc.
Category: homeopathic | Type: HUMAN OTC DRUG LABEL
Date: 20230608

ACTIVE INGREDIENTS: CONVALLARIA MAJALIS 4 [hp_X]/1 mL; APOCYNUM CANNABINUM ROOT 6 [hp_X]/1 mL; SUS SCROFA ARTERY 8 [hp_X]/1 mL; PORK HEART 8 [hp_X]/1 mL; THYROID 8 [hp_X]/1 mL; ADONIS VERNALIS WHOLE 10 [hp_X]/1 mL; SELENICEREUS GRANDIFLORUS STEM 12 [hp_X]/1 mL; DIGITALIS 12 [hp_X]/1 mL; LYCOPUS VIRGINICUS WHOLE 12 [hp_X]/1 mL
INACTIVE INGREDIENTS: WATER; ALCOHOL

Drug Facts:

ACTIVE INGREDIENTS:

(in each drop): 12.49% of Adonis Vernalis 10X, Arteria Suis 8X, Cactus Grandiflorus 12X, Convallaria Majalis 4X, Digitalis Purpurea 12X, Heart (Suis) 8X, Lycopus Virginicus 12X, Thyroidinum (Suis) 8X; 0.10% of Apocynum Cannabinum 6X.

INDICATIONS:

May temporarily relieve difficulty breathing after walking, tiredness, feeling as if you can't breathe, and profuse perspiration.**

**Claims based on traditional homeopathic practice, not accepted medical evidence. Not FDA evaluated.

WARNINGS:

If pregnant or breastfeeding, ask a health professional before use.

Keep out of reach of children. In case of overdose, get medical help or contact a Poison Control Center right away.

Do not use if tamper evident seal is broken or missing.

Store in a cool, dry place.

Keep out of reach of children. In case of overdose, get medical help or contact a Poison Control Center right away.

DIRECTIONS:

Adults and children 5 to 10 drops orally, 3 times daily or as otherwise directed by a health care professional. If symptoms persist for more than 7 days, consult your health care professional. Consult a physician for use in children under 12 years of age.

INDICATIONS:

May temporarily relieve difficulty breathing after walking, tiredness, feeling as if you can't breathe, and profuse perspiration.**

**Claims based on traditional homeopathic practice, not accepted medical evidence. Not FDA evaluated.

INACTIVE INGREDIENTS:

Demineralized water, 20% Ethanol.

QUESTIONS:

Dist. by Energique, Inc.
201 Apple Blvd.
Woodbine, IA 51579 800.869.8078

PACKAGE LABEL DISPLAY:

ENERGIQUE
SINCE 1987
HOMEOPATHIC REMEDY
CARDIOPAR
1 fl. oz. (30 ml)